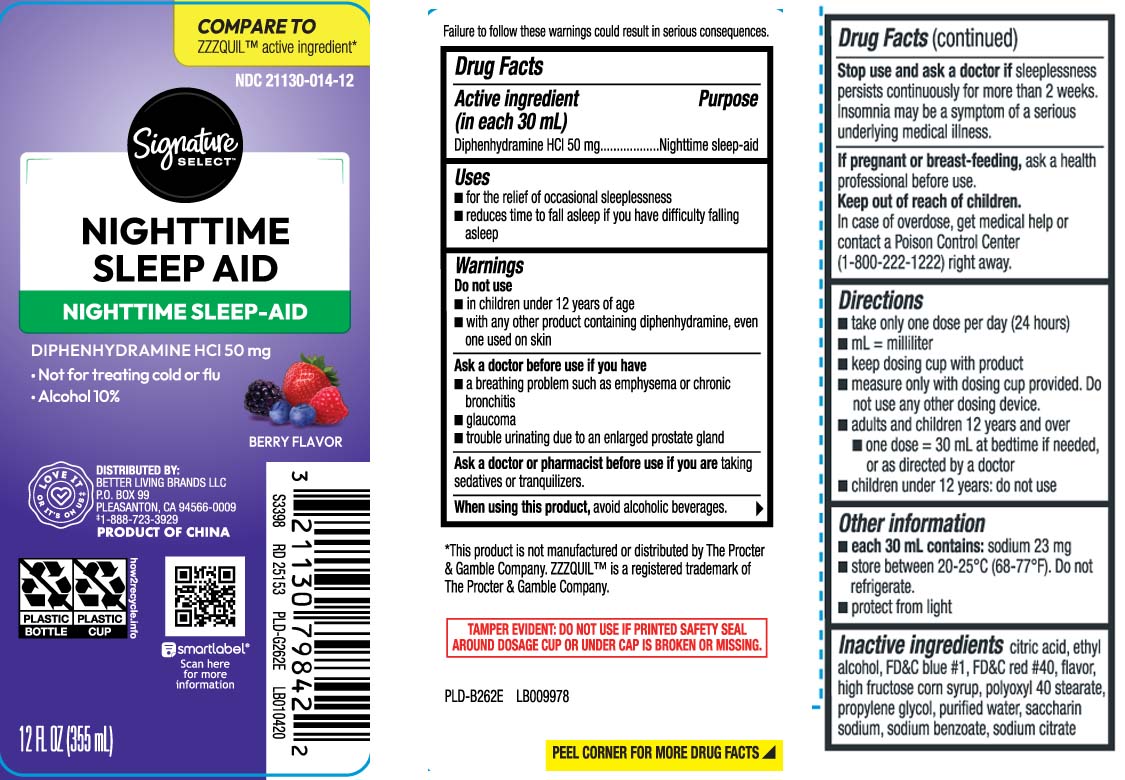 DRUG LABEL: EZ Nite Sleep
NDC: 21130-014 | Form: LIQUID
Manufacturer: Safeway, Inc.
Category: otc | Type: HUMAN OTC DRUG LABEL
Date: 20250707

ACTIVE INGREDIENTS: DIPHENHYDRAMINE HYDROCHLORIDE 50 mg/30 mL
INACTIVE INGREDIENTS: ANHYDROUS CITRIC ACID; PROPYLENE GLYCOL; POLYOXYL STEARATE 40; WATER; SODIUM BENZOATE; SACCHARIN SODIUM ANHYDROUS; TRISODIUM CITRATE DIHYDRATE; HIGH FRUCTOSE CORN SYRUP; FD&C BLUE NO. 1; FD&C RED NO. 40; ALCOHOL

Drug Facts

Active ingredient (in each 30 mL)

Diphenhydramine HCl 50 mg

Purpose

Nighttime sleep-aid

Uses

- for the relief of occasional sleeplessness
- reduces time to fall asleep if you have difficulty falling asleep

Warnings

Do not use

- with any other product containing diphenhydramine, even one used on skin
- for children under 12 years of age

Ask a doctor before use if you have

- breathing problem such as asthma emphysema or chronic bronchitis
- glaucoma
- trouble urinating due to an enlarged prostate gland

Ask a doctor or pharmacist before use if you are

taking sedatives or tranquilizers.

When using this product

- avoid alcoholic beverages.

Stop use and ask a doctor if

sleeplessness persists continuously for more than 2 weeks. Insomnia may be a symptom of serious underlying medical illness.

If pregnant or breast-feeding,

ask a health professional before use.

Keep out of reach of children.

Overdose warning: In case of overdose, get medical help or contact a Poison Control Center (1800-222-1222) right away.

Directions

- take only one dose per day (24 hours)
- mL= milliliter
- keep dosing cup with product
- measure only with dosing cup provided. Do not use any other dosing device
- adults and children 12 years and over
  - one dose=30mL at bedtime if needed, or as directed by a doctor
- children under 12 years do not use

Other information

- each 30 mL contains: sodium 23 mg
- store between 20-25ºC (68-77ºF). Do not refrigerate
- protect from light

Inactive ingredients

citric acid, ethyl alcohol, FD&C blue #1, FD&C red #40, flavor, high fructose corn syrup, polyoxyl 40 stearate, propylene glycol, purified water, saccharin sodium, sodium benzoate, sodium citrate dihydrate

Principal Display Panel

COMPARE TO ZZZQUIL™ active ingredient*

NIGHTTIME SLEEP AID

NIGHTTIME SLEEP-AID

DIPHENHYDRAMINE HCI 50 mg

- Not for treating cold or flu
- 10 % alcohol

BERRY FLAVOR

fl oz (mL)

Failure to follow these warnings could results in serious consequences.

TAMPER EVIDENT: DO NOT USE IF PRINTED SAFETY SEAL AROUND DOSAGE CUP OR UNDER CAP IS BROKEN OR MISSING.

*This product is not manufactured or distributed by The Procter & Gamble Company. ZZZQUI™ is a registered trademark of The Proctor & Gamble Company.

DISTRIBUTED BY

BETTER LIVING BRANDS LLC

P.O. BOX 99,

PLEASANTON, CA 94566-0009

Package Label

SIGNATURE SELECT Nighttime Sleep Aid Berry Flavor